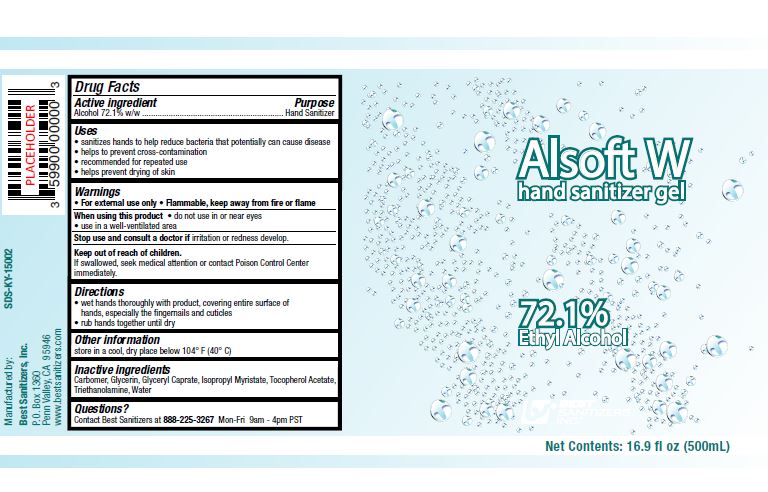 DRUG LABEL: Alsoft W hand sanitizer
NDC: 59900-351 | Form: GEL
Manufacturer: Best Sanitizers, Inc
Category: otc | Type: HUMAN OTC DRUG LABEL
Date: 20241205

ACTIVE INGREDIENTS: ALCOHOL 78.3 mL/100 mL
INACTIVE INGREDIENTS: GLYCERIN; ISOPROPYL MYRISTATE; GLYCERYL CAPRATE; TROLAMINE; CARBOMER HOMOPOLYMER, UNSPECIFIED TYPE; .ALPHA.-TOCOPHEROL ACETATE; WATER

Alsoft W 59900-351

Active ingredient

Alcohol 72.1 w/w

Purpose

Hand Sanitizer

Uses

- sanitizes hands to help reduce bacteria that potentially can cause disease
- helps to prevent cross-contamination
- recommended for repeated use
- helps pevent drying of skin

Warnings

- For external use only
- Flammable, keep away from fire or flame

When using this product

- do not use in or near eyes
- use in a well-ventilated area

Stop use and consult a doctor ifirritation or redness develop.

Keep out of reach of children.

If swallowed, seek medical attention or contact Poison Control Center immediately.

Directions

- wet hands thoroughly with product, covering entire surface of hands, especially the fingernails and cuticles
- rub hands together until dry

Other information

store in a cool, dry place below 104 F (40 C)

Inactive ingredients

Carbomer, Glycerin, Glyceryl Caprate, Isopropyl Myristate, Tocopherol Acetate, Triethanolamine, Water

Questions?

Contact Best Sanitizers at 888-225-3267Mon-Fri 9 am - 4 pm PST

PACKAGE LABEL

Alsoft W

hand sanitizer gel

72.1%

Ethyl Alcohol

Net Contents: 16.9 fl oz (500 mL)